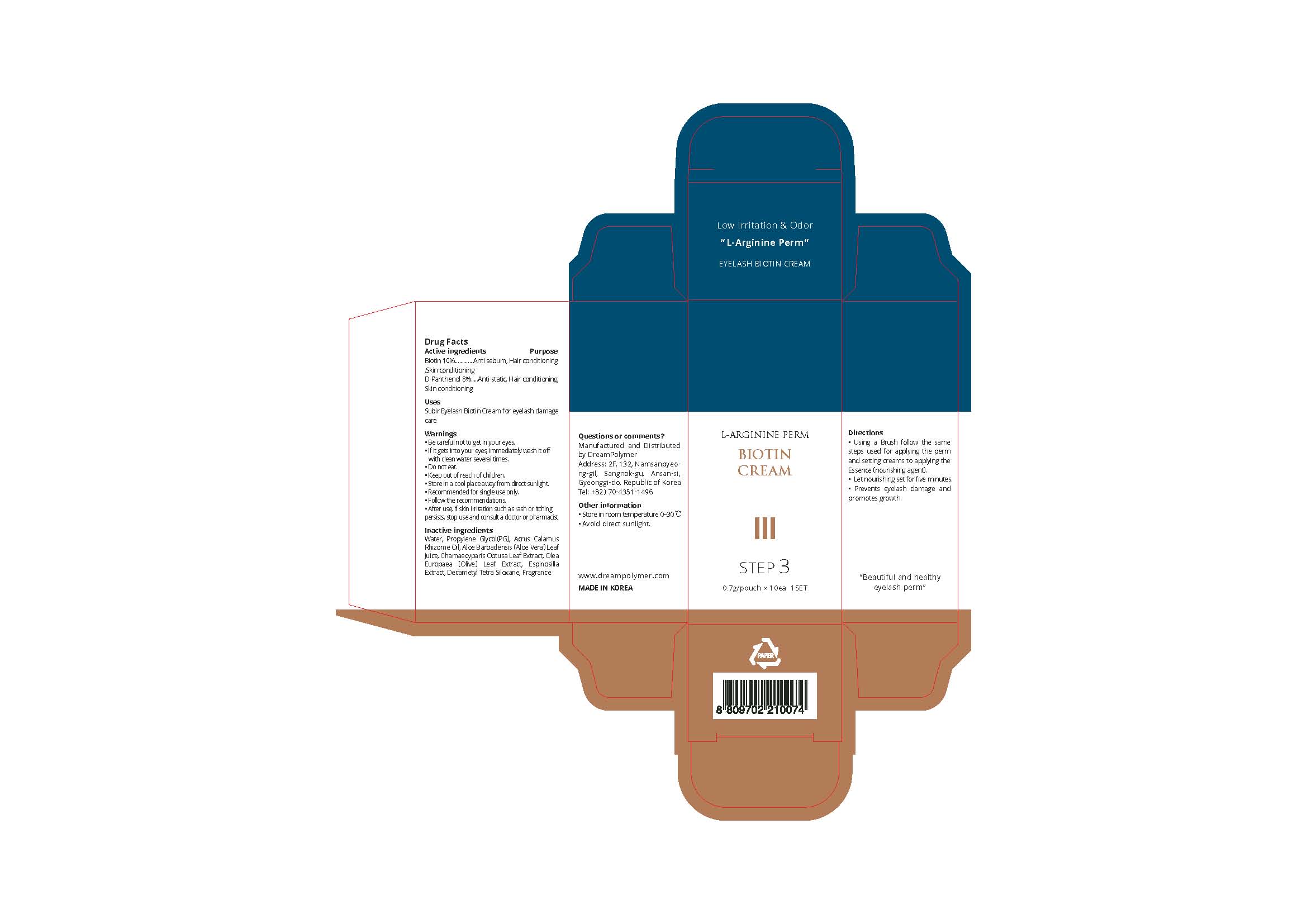 DRUG LABEL: SUBIR EYELASH
NDC: 81716-004 | Form: CREAM
Manufacturer: Dream Polymer
Category: otc | Type: HUMAN OTC DRUG LABEL
Date: 20210330

ACTIVE INGREDIENTS: BIOTIN 0.07 g/0.7 g
INACTIVE INGREDIENTS: Water; Propylene Glycol; OLEA EUROPAEA LEAF; CHAMAECYPARIS OBTUSA LEAF

Active Ingredient(s)

Biotin 10%

D-Panthenol 8%

Purpose

Anti-static, Hair conditioning, Skin conditioning

Use

Subir Eyelash Biotin Cream for eyelash damage care

Warnings

• Be careful not to get in your eyes.
• If it gets into your eyes, immediately wash it off with clean water several times.
• Wear appropriate gloves during the procedure.
• Do not eat.
• Keep out of reach of children.
• Store in a cool place away from direct sunlight.
• Recommended for single use only.
• For professional use only.
• Follow the recommendations.
• After use, if skin irritation such as rash or itching persists, stop use and consult a doctor or pharmacist

 Keep out of reach of children.

Directions

• Using a Brush follow the same steps used for applying the perm and setting creams to applying the Essence (nourishing agent).
• Let nourishing set for five minutes.
• Prevents eyelash damage and promotes growth.

Other information

・ Store in room temperature 0~30℃
・ Avoid direct sunlight.

Inactive ingredients

Water, Propylene Glycol(PG), Acrus Calamus Rhizome Oil, Aloe Barbadensis (Aloe Vera) Leaf Juice, Chamaecyparis Obtusa Leaf Extract, Olea Europaea (Olive) Leaf Extract, Espinosilla Extract, Decametyl Tetra Siloxane, Fragrance